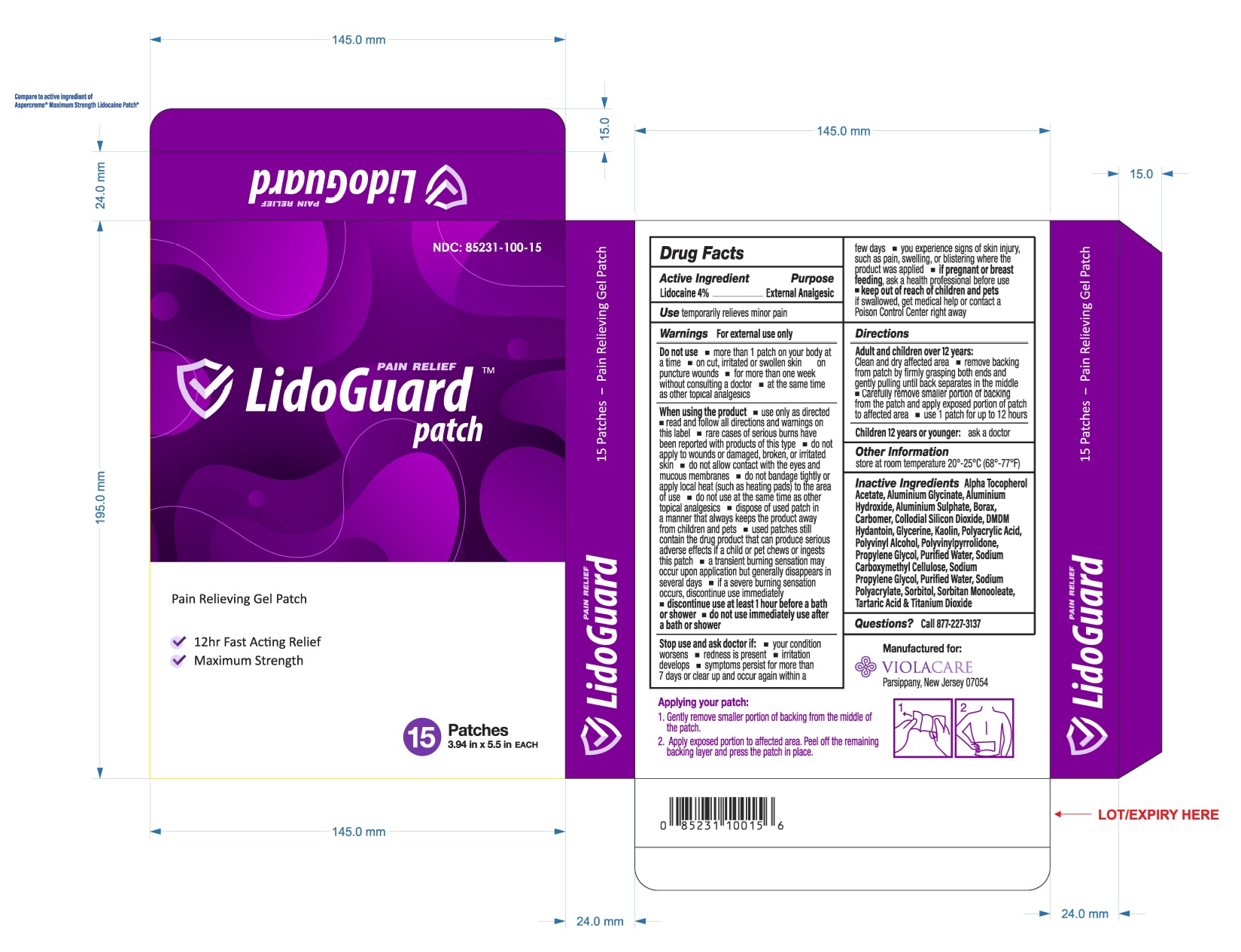 DRUG LABEL: LIDOGUARD
NDC: 85231-100 | Form: PATCH
Manufacturer: ViolaCare, Inc.
Category: otc | Type: HUMAN OTC DRUG LABEL
Date: 20250530

ACTIVE INGREDIENTS: LIDOCAINE 4 g/100 g
INACTIVE INGREDIENTS: ALPHA-TOCOPHEROL ACETATE; ALUMINUM HYDROXIDE; CARBOMER 940; DMDM HYDANTOIN; GLYCERIN; KAOLIN; POLYACRYLIC ACID (250000 MW); POLYVINYL ALCOHOL (100000 MW); WATER; SODIUM POLYACRYLATE (8000 MW); SORBITOL; SORBITAN MONOOLEATE; TARTARIC ACID; TITANIUM DIOXIDE

LidoGuardTMPain Relief Patch
Lidocaine 4% External Analgesic
Pain Relieving Gel Patch
For Temporarily Relieves Minor Pain

Active Ingredients

Lidocaine 4%

Purpose

External Anesthetic

Uses:

Temporarily relieves minor pain

Warnings:

For external use only

Do not use

- More than 1 patch on your body at a time
- On cut, irritated or swollen skin on puncture wounds
- For more than one week without consulting a doctor
- At the same time as other topical analgesics

When using the product

- Use only as directed
- Read and follow all directions and warnings on this label
- Rare cases of serious burns have been reported with products of this type
- Do not apply to wounds or damaged, broken, or irritated skin
- Do not allow contact with the eyes and mucous membranes
- Do not bandage tightly or apply local heat (such as heating pads) to the area of use
- Do not use at the same time as other topical analgesics
- Dispose of used patch in a manner that always keeps the product away from children and pets
- Used patches still contain the drug product that can produce serious adverse effects if a child or pet chews or ingests this patch
- A transient burning sensation may occur upon application but generally disappears in several days
- If a severe burning sensation occurs, discontinue use immediately
- Discontinue use at least 1 hour before a bath or shower
- Do not use immediately use after a bath or shower

Stop use and ask doctor if

- Your condition worsens
- Redness is present
- Irritation develops
- Symptoms persist for more than 7 days or a clear up and occur again within a few days
- You experience signs of skin injury, such as pain, swelling, or blistering where the product was applied

Pregnancy or breast feeding section

If pregnant or breast-feeding, ask a health professional before use.

Keep out of reach of children and pets.

If swallowed, get medical help or contact a Poison Control Center right away.

Directions

Adult and children over 12 years:

- Clean and dry affected area
- Remove backing from patch by firmly grasping both ends and gently pulling until back separates in the middle
- Carefully remove smaller portion of backing from the patch and apply exposed portion of patch to affected area
- Use 1 patch for up to 12 hours

Children 12 years or younger:Ask a doctor

Other information:

Store at room temperature 20° - 25°C (68°-77°F)

INACTIVE INGREDIENT

Inactive Ingredients: Alpha Tocopherol Acetate, Aluminum Glycinate, Aluminum Hydroxide, Aluminum Sulphate, Borax, Carbomer, Collodial Silicon Dioxide, DMDM Hydantoin, Glycerin, Kaolin, Polyacrylic Acid, Polyvinyl Alcohol, Polyvinylpyrrolidone, Propylene Glycol, Purified Water, Sodium Carboxymethyl Cellulose, Sodium Propylene Glycol, Sodium Polyacrylate, Sorbitol, Sorbitan Monooleate, Tartric Acid & Titanium Dioxide

Question Section

Questions? Call 877-227-3137

PRINCIPAL DISPLAY PANEL

NDC 85231-100-15

LidoGuard Pain Relief Patch

Pain Relieving Gel Patch

12hr Fast Acting Relief

Maximum Strength

15 Patches - Pain Relieving Gel Patch

15 Patches

3.94 in x 5.5 in EACH

Packaged For:

ViolaCare Inc.

Parsippany, New Jersey, 07054